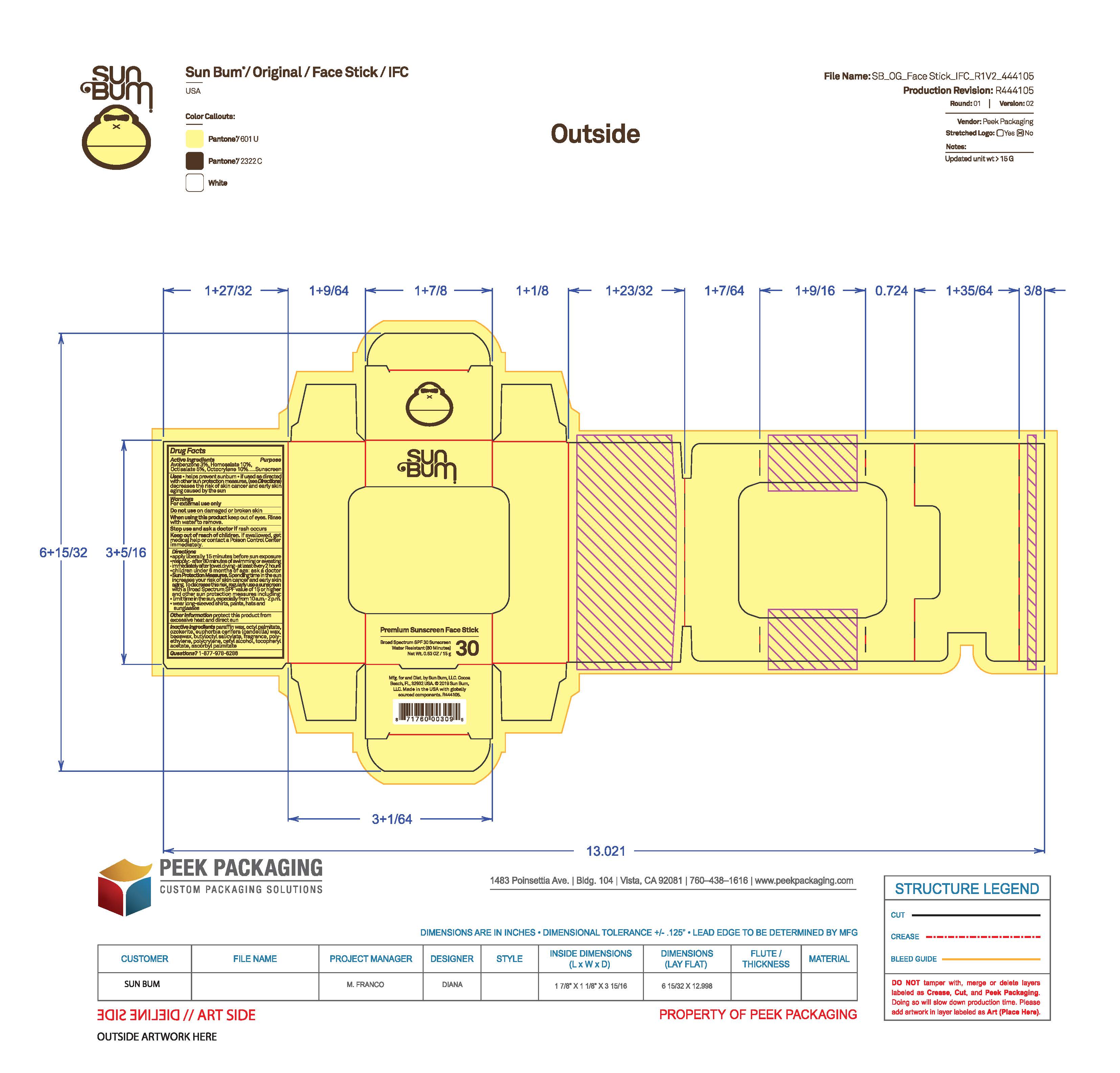 DRUG LABEL: Sun Bum Premium Sunscreen Face Stick Broad Spectrum SPF 30 Sunscreen - Pegged
NDC: 69039-834 | Form: STICK
Manufacturer: Sun Bum, LLC
Category: otc | Type: HUMAN OTC DRUG LABEL
Date: 20250902

ACTIVE INGREDIENTS: OCTISALATE 50 mg/1 g; OCTOCRYLENE 100 mg/1 g; AVOBENZONE 30 mg/1 g; HOMOSALATE 100 mg/1 g
INACTIVE INGREDIENTS: POLYESTER-8 (1400 MW, CYANODIPHENYLPROPENOYL CAPPED); CERESIN; .ALPHA.-TOCOPHEROL ACETATE; PARAFFIN; OCTYL PALMITATE; ASCORBYL PALMITATE; BEESWAX; BUTYLOCTYL SALICYLATE; POLYETHYLENE; CETYL ALCOHOL; EUPHORBIA CERIFERA (CANDELILLA) WAX

Sun Bum Premium Sunscreen Face Stick Broad Spectrum SPF 30 Sunscreen - Pegged

Active Ingredients

Avobenzone 3%, Homosalate 10%, Octisalate 5%, Octocrylene 10%

Purpose

Sunscreen

Uses

• helps prevent sunburn • if used as directed with other sun protection measures, (see Directions) decreases the risk of skin cancer and early skin aging caused by the sun

Warnings

For external use only

Do not use on damaged or broken skin

When using this product keep out of eyes. Rinse with water to remove.

Stop use and ask a doctor if rash occurs

Keep out of reach of children. If swallowed, get medical help or contact a Poison Control Center immediately.

Warnings

Keep Out Of Reach Of Children

Directions

• apply liberally 15 minutes before sun exposure

• reapply: • after 80 minutes of swimming or sweating • immediately after towel drying • at least every 2 hours

• children under 6 months of age: ask a doctor

• Sun Protection Measures. Spending time in the sun increases your risk of skin cancer and early skin aging. To decrease this risk, regularly use a sunscreen with a Broad Spectrum SPF value of 15 or higher and other sun protection measures including:

• limit time in the sun, especially from 10 a.m.- 2 p.m.

• wear long-sleeved shirts, pants, hats and sunglasses

Directions

• apply liberally 15 minutes before sun exposure

Other Information

protect this product from excessive heat and direct sun

Inactive Ingredients

paraffin wax, octyl palmitate, ozokerite, euphorbia cerifera (candelilla) wax, beeswax, butyloctyl salicylate, fragrance, polyethylene, polycrylene, cetyl alcohol, tocopheryl acetate, ascorbyl palmitate

Questions?

1-877-978-6286